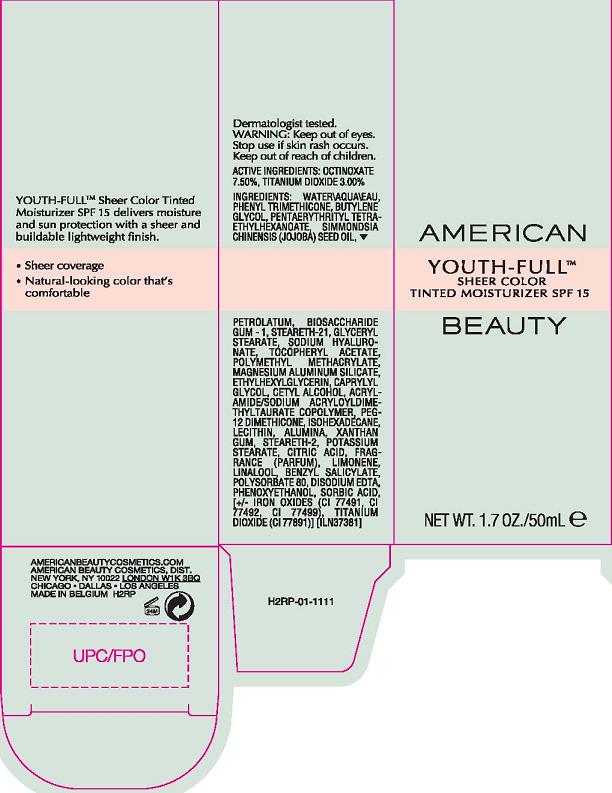 DRUG LABEL: YOUTH FULL TINTED MOISTURIZER
NDC: 68759-003 | Form: LIQUID
Manufacturer: AMERICAN BEAUTY COSMETICS
Category: otc | Type: HUMAN OTC DRUG LABEL
Date: 20110707

ACTIVE INGREDIENTS: OCTINOXATE 7.5 mL/100 mL; TITANIUM DIOXIDE 3 mL/100 mL
INACTIVE INGREDIENTS: WATER; PHENYL TRIMETHICONE; BUTYLENE GLYCOL; JOJOBA OIL; PETROLATUM; BIOSACCHARIDE GUM-1; STEARETH-21; GLYCERYL MONOSTEARATE; HYALURONATE SODIUM; ALPHA-TOCOPHEROL ACETATE; MAGNESIUM ALUMINUM SILICATE; ETHYLHEXYLGLYCERIN; CAPRYLYL GLYCOL; CETYL ALCOHOL; ISOHEXADECANE; LECITHIN, SOYBEAN; ALUMINUM OXIDE; XANTHAN GUM; STEARETH-2; POTASSIUM STEARATE; CITRIC ACID MONOHYDRATE; POLYSORBATE 80; EDETATE DISODIUM; PHENOXYETHANOL; SORBIC ACID; FERRIC OXIDE RED

ACTIVE INGREDIENT

ACTIVE INGREDIENTS: OCTINOXATE 7.50% [] TITANIUM DIOXIDE 3.00%

INACTIVE INGREDIENT

INGREDIENTS: WATER [] PHENYL TRIMETHICONE [] BUTYLENE GLYCOL [] PENTAERYTHRITYL TETRAETHYLHEXANOATE [] SIMMONDSIA CHINENSIS (JOJOBA) SEED OIL [] PETROLATUM [] BIOSACCHARIDE GUM - 1 [] STEARETH-21 [] GLYCERYL STEARATE [] SODIUM HYALURONATE [] TOCOPHERYL ACETATE [] POLYMETHYL METHACRYLATE [] MAGNESIUM ALUMINUM SILICATE [] ETHYLHEXYLGLYCERIN [] CAPRYLYL GLYCOL [] CETYL ALCOHOL [] ACRYLAMIDE/SODIUM ACRYLOYLDIMETHYLTAURATE COPOLYMER [] PEG-12 DIMETHICONE [] ISOHEXADECANE [] LECITHIN [] ALUMINA [] XANTHAN GUM [] STEARETH-2 [] POTASSIUM STEARATE [] CITRIC ACID [] FRAGRANCE (PARFUM) [] LIMONENE [] LINALOOL [] BENZYL SALICYLATE [] POLYSORBATE 80 [] DISODIUM EDTA [] PHENOXYETHANOL [] SORBIC ACID [] [+/- IRON OXIDES (CI 77491, CI 77492, CI 77499) [] TITANIUM DIOXIDE (CI 77891)

WARNINGS

WARNING: KEEP OUT OF EYES. STOP USE IF IRRITATION OCCURS. KEEP OUT OF REACH OF CHILDREN

PACKAGE LABEL

PRINCIPAL DISPLAY PANEL:
AMERICAN
BEAUTY
YOUTH-FULL
SHEER COLOR
TINTED MOISTURIZER
SPF 15
NT WT 1.7 OZ./ 50 ML
AMERICAN BEAUTY COSMETICS, DIST
NEW YORK, NY 10022